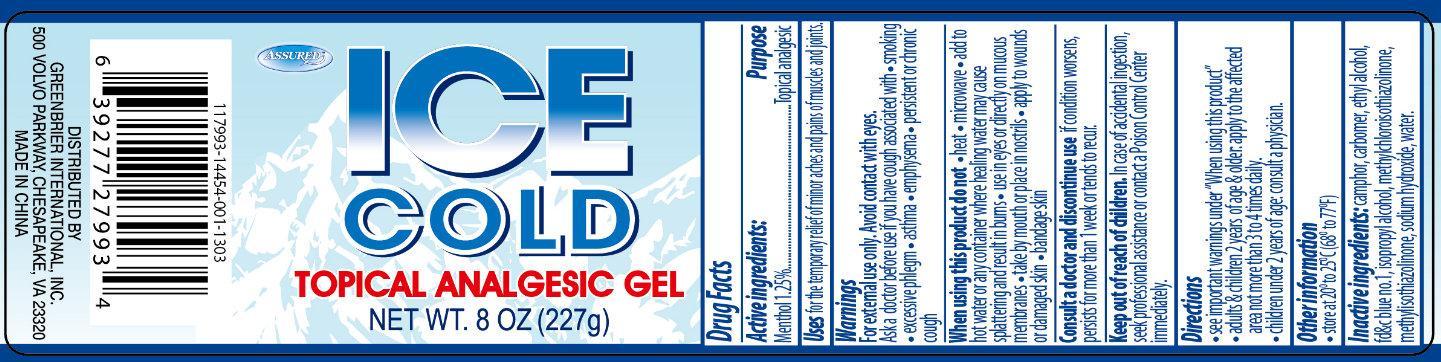 DRUG LABEL: ASSURED ICE COLD TOPICAL ANALGESIC
                
NDC: 33992-7994 | Form: GEL
Manufacturer: Greenbrier International, Inc.
Category: otc | Type: HUMAN OTC DRUG LABEL
Date: 20130327

ACTIVE INGREDIENTS: MENTHOL 1.25 g/100 g
INACTIVE INGREDIENTS: CAMPHOR (NATURAL); ALCOHOL; FD&C BLUE NO. 1; ISOPROPYL ALCOHOL; METHYLCHLOROISOTHIAZOLINONE; SODIUM HYDROXIDE; WATER

ASSURED ICE COLD TOPICAL ANALGESIC GEL

Active Ingredient

Menthol 1.25%

Purpose

Topical Analgesic

Uses

for the temporary relief of minor aches and pains of muscles and joints

Warnings

For external use only. Avoid contact with eyes.

Ask a doctor before use if you have cough associated with

- smoking
- excessive phlegm
- asthma
- emphysema
- persistent or chronic cough

When using this product do not

- heat
- microwave
- add to hot water or any container where healing water may cause splattering and result in burns
- use in eyes or directly on mucous membranes
- take by mouth or place in nostrils
- apply to wounds or damaged skin
- bandage skin

Consult a doctor and discontinue use

if condition worsens, persist for more than 1 week or tends to recur

Keep out of reach of children.

In case of accidental ingestion, seek professional assistance or contact a Poison Control Center immediately.

Directions

- see important warnings under "When using this product"
- adults and children 2 years of age and older: apply to the affected area not more than 3 to 4 times daily
- children under 2 years of age: consult a physician.

Other information

store at 20 to 25 degreesC (68 to 77degrees F)

Inactive Ingredients

camphor, carbomer, ethyl alcohol, FDandC blue no.1, isopropyl alcohol, methylchloroisothiasolinone, methylisothiazolinone, sodium hydroxide, water.

PACKAGE LABEL

Assured ICE COLD

Topical Analgesic Gel

Net wt 8oz (227g)

DISTRIBUTED BY:

GREENBRIER INTERNATIONAL, INC.

CHESAPEAKE, VA 23320

MADE IN CHINA